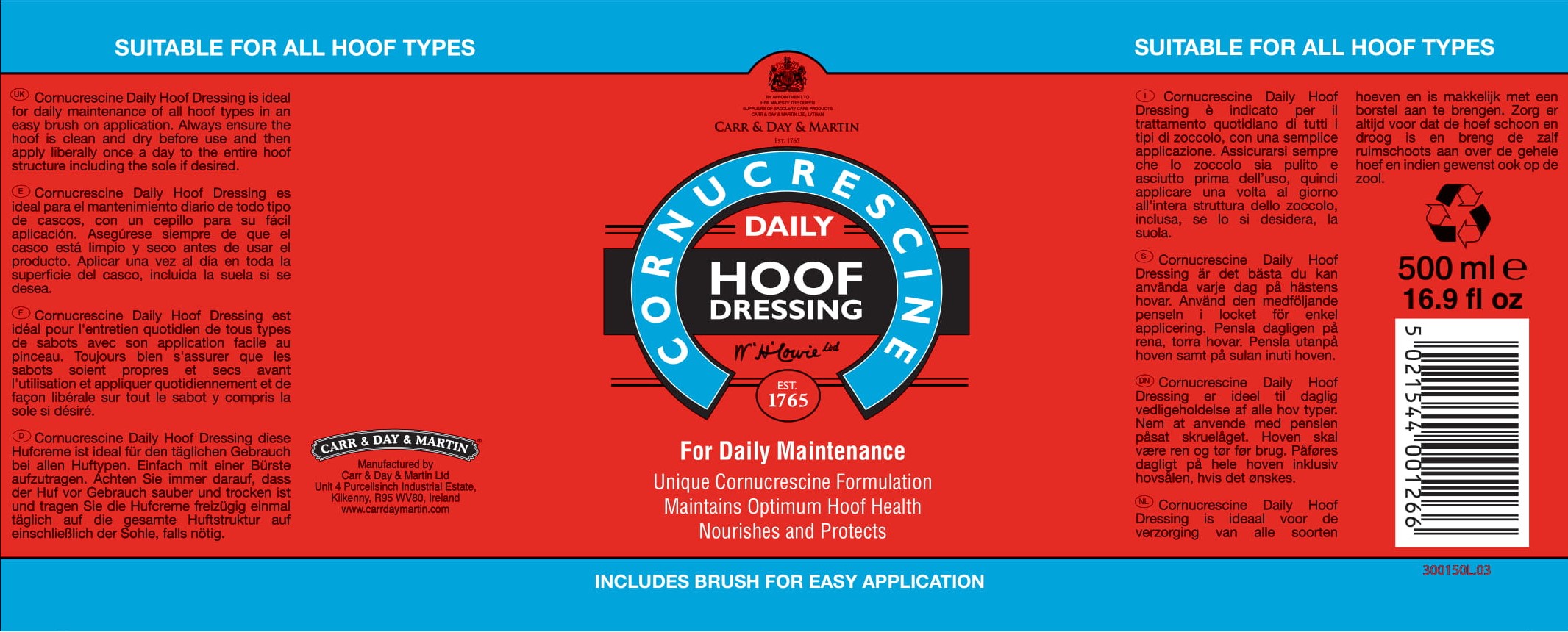 DRUG LABEL: Cornucrescine Daily Hoof Dressing
NDC: 43258-315 | Form: DRESSING
Manufacturer: Carr & Day & Martin Unlimited Company
Category: animal | Type: OTC ANIMAL DRUG LABEL
Date: 20250107

ACTIVE INGREDIENTS: PETROLATUM 731 g/1 L; Sassafras Oil 10.1 g/1 L
INACTIVE INGREDIENTS: ALCOHOL; LANOLIN; ALOE FEROX LEAF; WATER; MINERAL OIL; LIGHT MINERAL OIL

Cornucrescine Daily Hoof Dressing

INDICATIONS AND USAGE

For Daily Maintenance

Unique Cornucrescine Formulation

Maintains Optimum Hoof Health

Nourishes and Protects

INCLUDES BRUSH FOR EASY APPLICATION

DOSAGE AND ADMINISTRATION

Cornucrescine Daily Hoof Dressing is ideal for daily maintenance of all hoof types in an easy brush on application. Always ensure the hoof is clean and dry before use and then apply liberally once a day to the entire hoof structure including the sole if desired.

Manufactured by

CARR & DAY & MARTIN Unlimited Company

Unit 4 Purcellsinch Industrial Estate,

Kilkenny, R95 WV80, Ireland

www.carrdaymartin.com